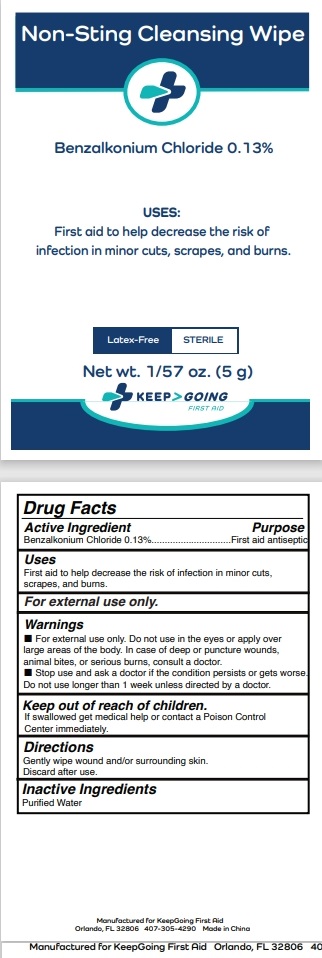 DRUG LABEL: Keep Going Non Sting Cleaning Wipe
NDC: 71734-343 | Form: SWAB
Manufacturer: JIANGMEN SHUIZIRUN SANITARY ARTICLES CO., LTD.
Category: otc | Type: HUMAN OTC DRUG LABEL
Date: 20240808

ACTIVE INGREDIENTS: BENZALKONIUM CHLORIDE 0.13 g/100 g
INACTIVE INGREDIENTS: WATER

DRUG FACTS

Active Ingredient

Benzalkonium Chloride .......... 0.13 %

Purpose

First Aid Antiseptic

Uses:

Cleans wounds to prvent infction. Kills bacteria on skin without soap and water.

Warnings

For external use only.

Do not use in the eyes. If irritation or redness occurs, stop use.

Keep out of reach of children. If swallowed get medical help or contact a Posion Control Center immediately.

Directions

Gently wipe wound and /or surrounding skin. Discard after use.

Inactive Ingredients:

Purified Water